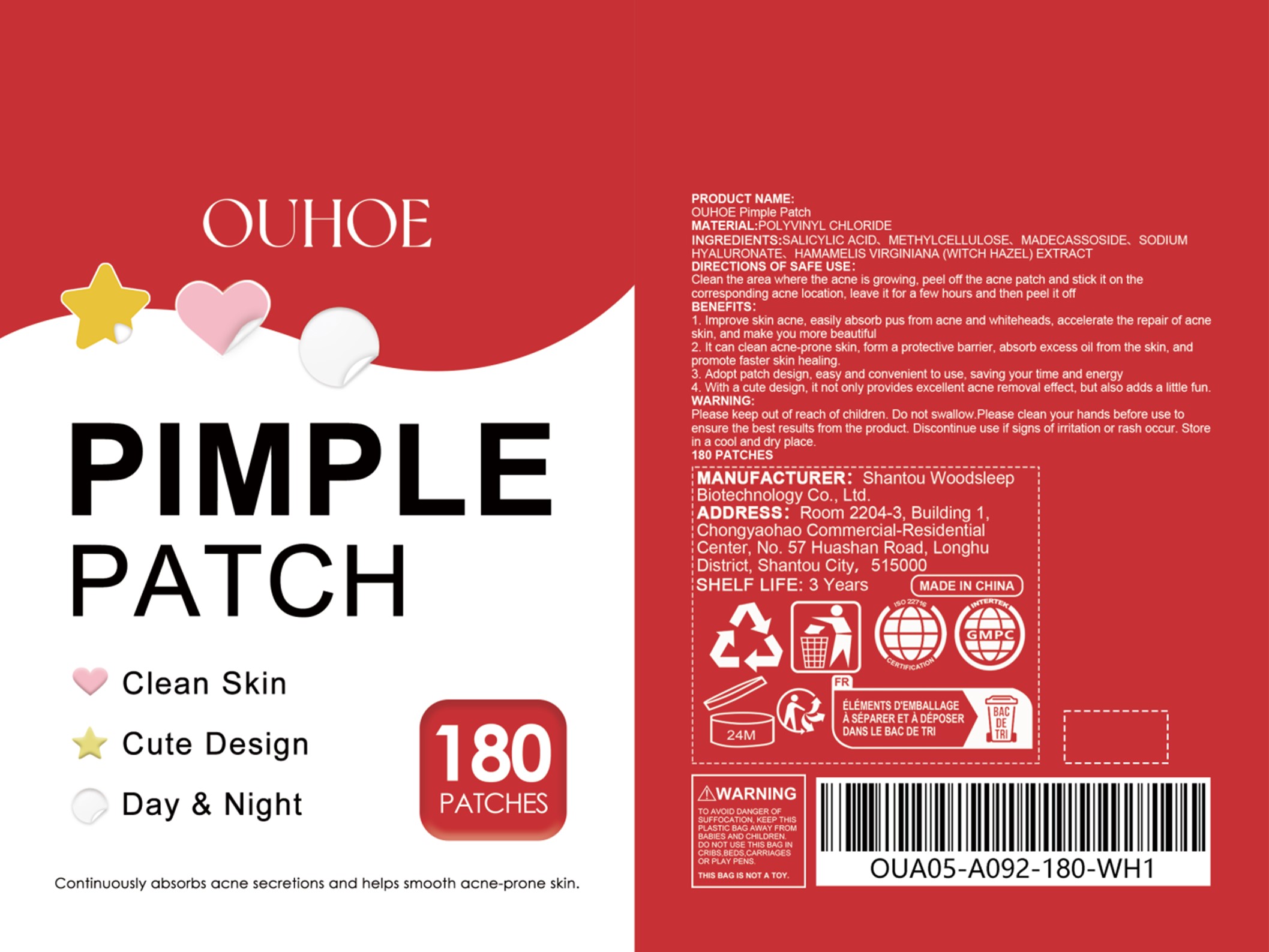 DRUG LABEL: OUHOE PIMPLE
NDC: 85053-001 | Form: PATCH
Manufacturer: Shantou Woodsleep Biotechnology Co., Ltd.
Category: otc | Type: HUMAN OTC DRUG LABEL
Date: 20251126

ACTIVE INGREDIENTS: SALICYLIC ACID 0.02 g/100 g
INACTIVE INGREDIENTS: HAMAMELIS VIRGINIANA WHOLE; METHYLCELLULOSE, UNSPECIFIED; HYALURONATE SODIUM; MADECASSOSIDE

Active Ingredient(s)

SAEICYLIC ACID

Purpose

1. it can quickly eliminate acne, prevent acne from leaving marks andscars on the face, and make your face smoother.

2. it can deeply hydrate acne and prevent acne areas from drying out

3. The ingredients are mild and suitable for all skin types, incudingdry,sensitive. oily. etc.

4. Easy to use, just apply it before going to bed to easily removeacne, helping to save your energy.

5 The cute shape helps you fall asleep with a pleasant and relaxedmood.

none

Warnings

Please keep out of reach of children. Do not swallow.Please clean your hands before use toensure the best results from the product., Discontinue use if signs of irritation or rash occur. Storein a cool and dry place.

none

none

Please keep out of reach of children

STORAGE AND HANDLING

Store in a cool and dry place

INACTIVE INGREDIENT

METHYLCELLULOSE、MADECASSOSIDE、SODIUM HYALURONATE、HAMAMELIS VIRGINIANA (WITCH HAZEL) EXTRACT

DIRECTIONS OF SAFE USE:

Clean the area where the acne is growing, peel off the acne patch and stick it on the corresponding acne location, leave it for a few hours and then peel it off

INDICATIONS AND USAGE

Clean the area where the acne is growing, peel off the acne patch and stick it on the corresponding acne location, leave it for a few hours and then peel it off